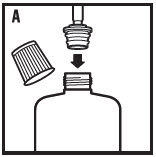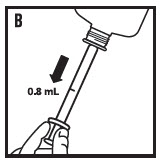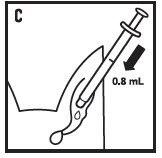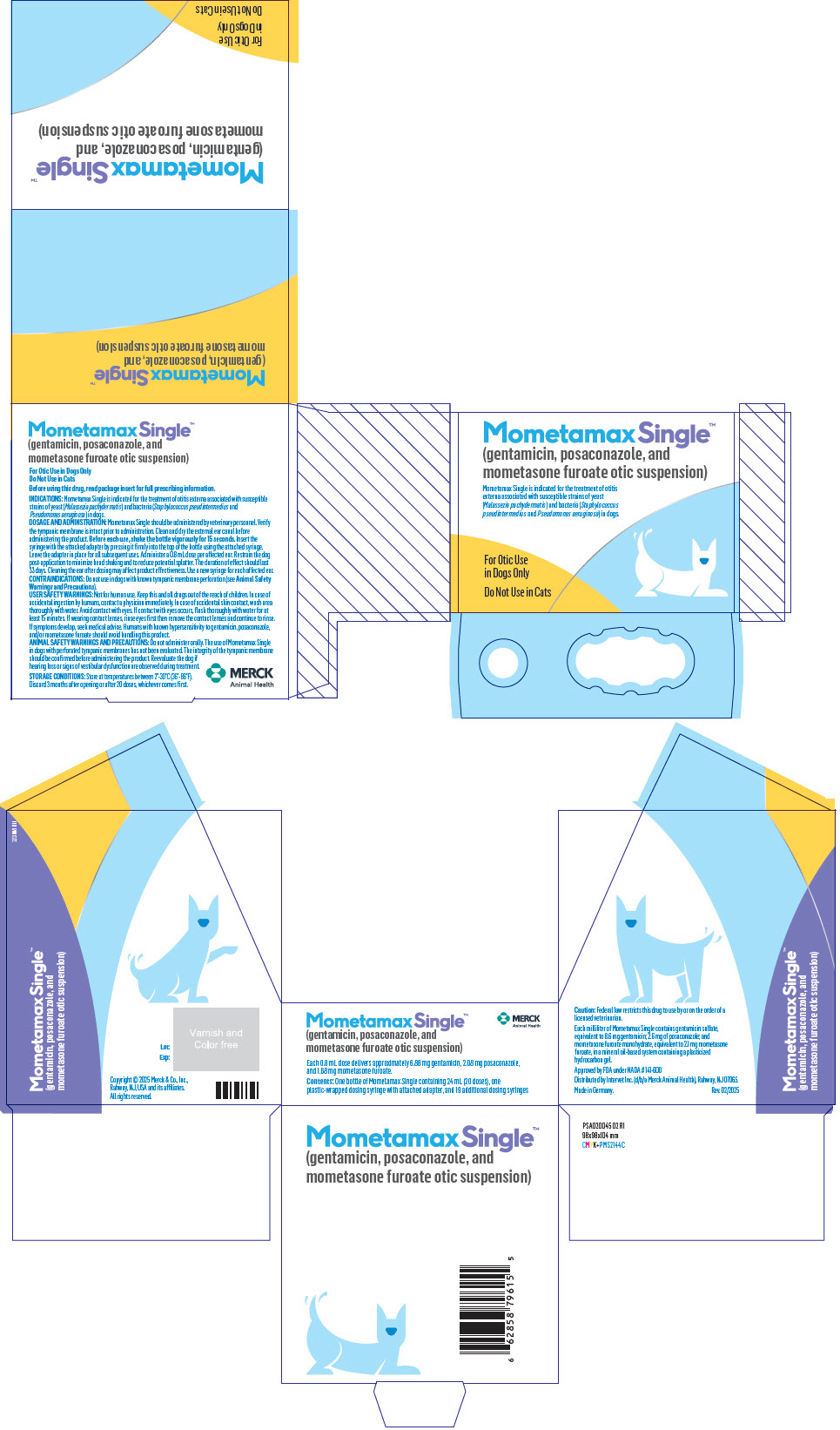 DRUG LABEL: Mometamax Single
NDC: 0061-5432 | Form: SUSPENSION
Manufacturer: Merck Sharp & Dohme Corp.
Category: animal | Type: PRESCRIPTION ANIMAL DRUG LABEL
Date: 20250506

ACTIVE INGREDIENTS: GENTAMICIN SULFATE 8.6 mg/1 mL; MOMETASONE FUROATE MONOHYDRATE 2.1 mg/1 mL; POSACONAZOLE 2.6 mg/1 mL

Mometamax Single™
(gentamicin, posaconazole, and
mometasone furoate otic suspension)

For Otic Use in Dogs Only

Do not use in cats

Antibacterial, antifungal, and anti-inflammatory

SAFE HANDLING WARNING

Caution: Federal law restricts this drug to use by or on the order of a licensed veterinarian.

DESCRIPTION:

Each milliliter of Mometamax Single contains gentamicin sulfate, equivalent to 8.6 mg gentamicin; 2.6 mg of posaconazole; and mometasone furoate monohydrate, equivalent to 2.1 mg mometasone furoate, in a mineral oil-based system containing a plasticized hydrocarbon gel.

A 0.8 mL dose volume of Mometamax Single delivers approximately 6.88 mg gentamicin, 2.08 mg posaconazole, and 1.68 mg mometasone furoate.

INDICATIONS:

Mometamax Single is indicated for the treatment of otitis externa associated with susceptible strains of yeast (Malassezia pachydermatis) and bacteria (Staphylococcus pseudintermedius and Pseudomonas aeruginosa) in dogs.

DOSAGE AND ADMINISTRATION:

Mometamax Single should be administered by veterinary personnel. The dose volume is 0.8 mL per affected ear.

Verify the tympanic membrane is intact prior to administration (see Contraindications, Animal Safety Warnings and Precautions).

1. Clean and dry the external ear canal before administering the product.
2. Shake bottle vigorously for 15 seconds.
3. Before first use, unwrap the syringe with the attached adapter.
4. Remove the cap from the bottle and insert the syringe with the attached adapter by pressing it firmly into the top of the bottle using the attached syringe (see figure A).
5. Invert the bottle and draw up 0.8 mL (see figure B).
6. Return the bottle to an upright position and remove the syringe from the adapter. Leave the adapter in place in the bottle for all subsequent uses.
7. Replace the cap on the bottle.
8. Place the tip of the syringe at the entrance of the external ear canal and administer the 0.8 mL dose (see figure C). The applied dose will flow into the ear canal.
9. Gently massage the base of the ear to ensure distribution of the product throughout the ear canal.
10. Restrain the dog post-application to minimize head shaking and to reduce potential splatter of product and accidental eye exposure in people and dogs.

11. Use a new syringe for each affected ear. Shake the bottle vigorously (with the cap on the bottle to prevent leakage) for 15 seconds before drawing up each new dose.
12. The duration of the effect should last 33 days. Cleaning the ear after dosing may affect product effectiveness.
13. Only twenty doses can be accurately withdrawn from the bottle. Discard the bottle 3 months after opening or after 20 doses, whichever comes first.

CONTRAINDICATIONS:

Do not use in dogs with known tympanic membrane perforation (see Animal Safety Warnings and Precautions).

Do not use in dogs with known or suspected hypersensitivity to gentamicin, posaconazole, or mometasone furoate.

WARNINGS AND PRECAUTIONS:

USER SAFETY WARNINGS:

Not for human use. Keep this and all drugs out of the reach of children. In case of accidental ingestion by humans, contact a physician immediately.

In case of accidental skin contact, wash area thoroughly with water.

Avoid contact with eyes. If contact with the eyes occurs, flush thoroughly with water for at least 15 minutes. If wearing contact lenses, rinse eyes first then remove the contact lenses and continue to rinse. If symptoms develop, seek medical advice.

Humans with known hypersensitivity to gentamicin, posaconazole, and/or mometasone furoate should avoid handling this product.

ANIMAL SAFETY WARNINGS AND PRECAUTIONS:

For otic use in dogs only. Do not use in cats.

Restrain the dog to minimize post-application head shaking. Reducing the potential for splatter of product helps prevent accidental eye exposure in people and dogs (see Dosage and Administration, User Safety Warnings).

The use of Mometamax Single in dogs with perforated tympanic membranes has not been evaluated. The integrity of the tympanic membrane should be confirmed before administering the product. Reevaluate the dog if hearing loss or signs of vestibular dysfunction are observed during treatment.

Do not administer orally.

Use of topical otic corticosteroids has been associated with adrenocortical suppression and iatrogenic hyperadrenocorticism in dogs (see Target Animal Safety).

Use with caution in dogs with impaired renal function. Gentamicin, one of the active ingredients in Mometamax Single, is associated with nephrotoxicity.

The safe use of Mometamax Single in dogs used for breeding purposes, during pregnancy, or during lactation has not been evaluated.

ADVERSE REACTIONS:

The following adverse reactions were reported during the course of a U.S. field study for treatment of otitis externa in dogs treated with Mometamax Single.

Frequency of Adverse Reactions by Treatment

Adverse Reaction | Mometamax Single (N=245) | Control (N=127)
Vomiting | 21 (8.6%) | 4 (3.1%)
Decreased appetite | 9 (3.7%) | 2 (1.6%)
Pruritus | 8 (3.3%) | 2 (1.6%)
Ear pruritus | 7 (2.9%) | 1 (0.8%)
Disorientation | 3 (1.2%) | 0 (0.0%)

CONTACT INFORMATION:

For technical information or to report a suspected adverse event, please contact Merck Animal Health at 1-800-224-5318 or https://www.merck-animal-health-usa.com. Safety Data Sheets (SDSs) can be found at https://www.merck.com/products/safety-data-sheets/#.

For additional information about reporting adverse drug experiences for animal drugs, contact FDA at 1-888-FDA-VETS or www.fda.gov/reportanimalae.

CLINICAL PHARMACOLOGY:

Mometamax Single is a combination of three active ingredients: gentamicin (antibacterial), posaconazole (antifungal), and mometasone furoate (steroidal anti-inflammatory). Gentamicin is an aminoglycoside bactericidal antibiotic which acts by binding to the 30S ribosomal subunit leading to inhibition of bacterial protein synthesis. Posaconazole is a triazole antifungal which selectively inhibits an enzyme involved in the biosynthesis of ergosterol. Mometasone furoate is a corticosteroid that binds to glucocorticoid receptors resulting in anti-inflammatory activity.

MICROBIOLOGY:

The compatibility and additive effect of each of the components in Mometamax Single was demonstrated in an in vitro non-interference study which utilized organisms collected from clinical cases of otitis externa in dogs. It determined that gentamicin and posaconazole inhibit the growth of bacteria and yeast commonly associated with otitis externa in dogs. No synergistic or antagonistic effect of the two antimicrobials was demonstrated. The addition of mometasone furoate to the combination did not impair antimicrobial activity.

In a field effectiveness study, each target microbial species (S. pseudintermedius, P. aeruginosa, and M. pachydermatis) was successfully treated in at least 10 or more dogs receiving Mometamax Single (see Effectiveness).

EFFECTIVENESS:

In a multicenter, well-controlled, randomized, double-masked field study, Mometamax Single was evaluated against a vehicle control in 372 dogs with otitis externa. Two hundred forty-five dogs were administered Mometamax Single, and 127 dogs were administered the vehicle control. Treatment (0.8 mL) was administered once on Day 0 to the affected ear(s). Prior to treatment, the ear(s) was cleaned with saline. Dogs were evaluated on Days 0, 7, 14, and 33. Blood work and urinalysis were obtained on Day 0 pre-treatment and on Day 33 at study completion. Four clinical signs associated with otitis externa were evaluated: erythema, swelling, ulceration, and exudate. Success was based on clinical improvement on Day 33. Of the 163 dogs included in the effectiveness evaluation, 80.5% of dogs administered Mometamax Single were successfully treated, compared to 19.6% of dogs administered the vehicle control (p<0.0001).

No clinically relevant treatment-related findings were noted in safety parameters.

TARGET ANIMAL SAFETY:

Margin of Safety Study: Mometamax Single was administered to 11- to 12-week-old puppies (4 dogs/sex/group) with 1×, 3×, or 5× the labeled dose of 0.8 mL/ear to both ears once every two weeks for a total of 3 doses on Days 1, 15, and 29. The control group received vehicle control on the same dosing schedule. No treatment-related effects on food consumption, body weights, clinical observations, physical examinations, otoscopic examinations, hearing assessments, electrocardiography, ophthalmic examinations, coagulation parameters, serum chemistry, urinalysis, fecal evaluations, or gross pathology were observed. Mometamax Single administration was associated with mild eosinopenia in the 3× and 5× groups and suppression of serum cortisol levels in the 1×, 3×, and 5× groups. On Day 30, two of eight 1× dogs and all 3× and 5× dogs had suppressed baseline cortisol levels. All control and 1× dogs had normal post-ACTH stimulation cortisol response levels. Seven of eight dogs in each of the 3× and 5× groups had suppressed ACTH stimulation responses but remained within the normal reference range.

The low baseline and post-ACTH test cortisol levels correlated with the pathology results of lower mean adrenal weights and mild atrophy of the adrenal cortex in the 3× and 5× groups. Histopathology demonstrated mild atrophy of the external auditory canal epidermis and mild atrophy of the external surface of the tympanic membrane in the 1×, 3×, and 5× groups. One male in the 3× group and one male in the 5× group had a minimal epidermal erosion/ulcer in the external auditory canal of one ear, whereas this finding was not noted in the control or 1× treatment groups.

STORAGE CONDITIONS:

Store at temperatures between 2°-30°C (36°-86°F). Discard 3 months after opening or after 20 doses, whichever comes first.

HOW SUPPLIED:
Mometamax Single (gentamicin, posaconazole, and mometasone furoate otic suspension) is supplied in a bottle containing 24 mL (20 doses) co-packaged with one plastic-wrapped dosing syringe with attached bottle adapter, and 19 additional dosing syringes.

Approved by FDA under NADA # 141-600

Made in Germany.

Distributed by Intervet Inc. (d/b/a Merck Animal Health), Rahway, NJ 07065.
Copyright © 2025 Merck & Co., Inc., Rahway, NJ, USA and its affiliates. All rights reserved.

Rev. 02/2025

223009 R8

PRINCIPAL DISPLAY PANEL - 24 mL Bottle Carton

Mometamax Single™
(gentamicin, posaconazole, and
mometasone furoate otic suspension)

Mometamax Single is indicated for the treatment of otitis
externa associated with susceptible strains of yeast
(Malassezia pachydermatis) and bacteria (Staphylococcus
pseudintermedius and Pseudomonas aeruginosa) in dogs.

For Otic Use
in Dogs Only

Do Not Use in Cats